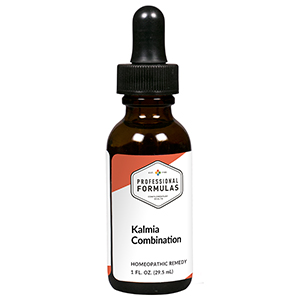 DRUG LABEL: Kalmia Combination
NDC: 63083-9228 | Form: LIQUID
Manufacturer: Professional Complementary Health Formulas
Category: homeopathic | Type: HUMAN OTC DRUG LABEL
Date: 20190815

ACTIVE INGREDIENTS: FERULA ASSA-FOETIDA RESIN 8 [hp_X]/29.5 mL; KALMIA LATIFOLIA LEAF 8 [hp_X]/29.5 mL; CAUSTICUM 10 [hp_X]/29.5 mL; COLCHICUM AUTUMNALE BULB 10 [hp_X]/29.5 mL; IRON 10 [hp_X]/29.5 mL; PSEUDOGNAPHALIUM OBTUSIFOLIUM WHOLE 10 [hp_X]/29.5 mL; LITHIUM BENZOATE 10 [hp_X]/29.5 mL; MERCURIC OXIDE 10 [hp_X]/29.5 mL; TOXICODENDRON PUBESCENS LEAF 10 [hp_X]/29.5 mL; FILIPENDULA ULMARIA ROOT 10 [hp_X]/29.5 mL
INACTIVE INGREDIENTS: ALCOHOL; WATER

R228

ACTIVE INGREDIENTS

Asafoetida 8X
Kalmia latifolia 8X
Causticum 10X
Colchicum autumnale 10X
Ferrum metallicum 10X
Gnaphalium polycephalum 10X
Lithium benzoicum 10X
Mercurius praecipitatus ruber 10X
Rhus toxicodendron 10X
Spiraea ulmaria 10X

QUESTIONS

Professional Formulas

PO Box 2034 Lake Oswego, OR 97035

INDICATIONS

For the temporary relief of minor pain, stiffness, or inflammation of joints or connective tissue.*

PURPOSE

*Claims based on traditional homeopathic practice, not accepted medical evidence. Not FDA evaluated.

WARNINGS

In case of overdose, get medical help or contact a poison control center right away.

Keep out of the reach of children.

PREGNANCY OR BREAST FEEDING

If pregnant or breastfeeding, ask a healthcare professional before use.

DIRECTIONS

Place drops under tongue 30 minutes before/after meals. Adults and children 12 years and over: Take 10 drops up to 3 times per day. Consult a physician for use in children under 12 years of age.

OTHER INFORMATION

Tamper resistant. If seal is broken, do not use. After opening, close container tightly and store at room temperature away from heat.

INACTIVE INGREDIENTS

40% ethanol, purified water.

LABEL

Est 1985

Professional Formulas

Complementary Health

Kalmia Combination

Homeopathic Remedy

1 FL. OZ. (29.5 mL)